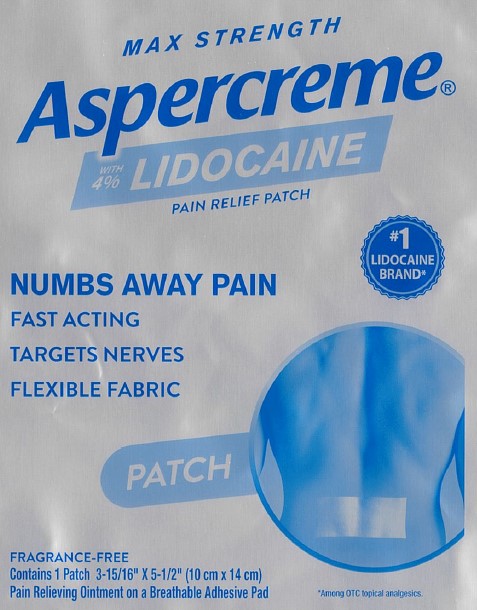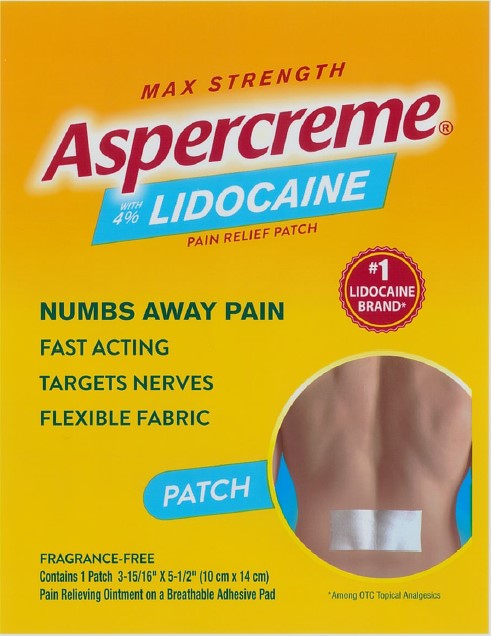 DRUG LABEL: Aspercreme
NDC: 62168-0584 | Form: PATCH
Manufacturer: Lead Chemical Co. Ltd.
Category: otc | Type: HUMAN OTC DRUG LABEL
Date: 20240125

ACTIVE INGREDIENTS: LIDOCAINE 246 mg/1 1
INACTIVE INGREDIENTS: DIHYDROXYALUMINUM AMINOACETATE ANHYDROUS; ALUMINUM HYDROXIDE; CARBOXYMETHYLCELLULOSE SODIUM, UNSPECIFIED FORM; GLYCERIN; METHYLPARABEN; NONOXYNOL-30; POLYSORBATE 80; PROPYLENE GLYCOL; SILICON DIOXIDE; TARTARIC ACID; TITANIUM DIOXIDE; UREA; WATER

Aspercreme Lidocaine Patch

Active ingredient – Lidocaine Patch US 1ct

Lidocaine 4%

Purpose – Lidocaine Patch US 1ct

Topical anesthetic

Use – Lidocaine Patch US 1ct

for the temporary relief of pain

Warnings – Lidocaine Patch US 1ct

For external use only

Do not use – Lidocaine Patch US 1ct

- on wounds or on irritated or damage skin
- more than 1 patch on your body at a time or with other topical analgesics at the same time
- with a heating pad

When using this product – Lidocaine Patch US 1ct

- use only as directed
- do not bandage tightly
- avoid contact with the eyes and mucous membranes
- do not expose the area to local heat or to direct sunlight

Stop use and ask a doctor if – Lidocaine Patch US 1ct

- condition worsens or symptoms persist for more than 7 days
- symptoms clear up and occur again within a few days
- redness is present or excessive skin irritation occurs
- you experience severe burning pain, swelling, or blistering where the product was applied

If pregnant or breast-feeding, – Lidocaine Patch US 1ct

ask a health professional before use.

Keep out of reach of children and pets. – Lidocaine Patch US 1ct

Used patches may still contain the drug product that can produce serious adverse effects if ingested by children or pets. If swallowed, get medical help or contact a Poison Control Center right away.

Directions – Lidocaine Patch US 1ct

• adults and children 12 years of age and older:

- clean and dry affected area
- remove backing from patch by firmly grasping both ends and gently pulling until backing separates in middle
- carefully remove smaller portion of backing from patch and apply exposed portion of patch to affected area
- once exposed portion of patch is positioned, carefully remove remaining backing to completely apply patch to affected area
- apply to the affected area not more than 3 to 4 times daily
- wash hands after applying or removing patch. Throw away the patch after folding sticky ends together.

• children under 12 years of age: ask a doctor

Inactive ingredients – Lidocaine Patch US 1ct

aluminum glycinate, aluminum hydroxide, cellulose gum, glycerin, methyl acrylate/2-ethylhexyl acrylate copolymer, methylparaben, nonoxynol-30, polyacrylic acid, polysorbate 80, propylene glycol, silica, sodium polyacrylate, tartaric acid, titanium dioxide, urea, water

Active ingredient – Lidocaine Patch Singles US 1ct

Lidocaine 4%

Purpose – Lidocaine Patch Singles US 1ct

Topical anesthetic

Use – Lidocaine Patch Singles US 1ct

For the temporarily relief of pain

Warnings – Lidocaine Patch Singles US 1ct

For external use only

Do not use – Lidocaine Patch Singles US 1ct

- on puncture wounds, cuts, irritated or swollen skin
- more than 1 patch on your body at a time or with other topical analgesics at the same time
- with a heating pad or apply local heat to the area of use

When using this product – Lidocaine Patch Singles US 1ct

- use only as directed
- do not bandage tightly
- avoid contact with the eyes
- dispose of used patch in manner that always keeps product away from children or pets. Used patches still contain the drug product that can produce serious adverse effects if a child or pet chews or ingests this patch.

Stop use and ask a doctor if – Lidocaine Patch Singles US 1ct

- condition worsens or symptoms persist for more than 7 days
- symptoms clear up and occur again within a few days
- redness or irritation develops
- you experience signs of skin injury, such as pain, swelling, or blistering where the product was applied

If pregnant or breast feeding, – Lidocaine Patch Singles US 1ct

ask a health professional before use.

Keep out of reach of children and pets. – Lidocaine Patch Singles US 1ct

If swallowed, get medical help or contact a Poison Control Center right away.

Directions – Lidocaine Patch Singles US 1ct

adults and children over 12 years of age and older:

- clean and dry affected area
- remove backing from patch by firmly grasping both ends and gently pulling until backing separates in middle
- carefully remove smaller portion of backing from patch and apply exposed portion of patch to affected area
- once exposed portion of patch is positioned, carefully remove remaining backing to completely apply patch to affected area
- use 1 patch at a time and not more than 3 to 4 times daily

children under 12 years of age: consult a doctor

Inactive ingredients – Lidocaine Patch Singles US 1ct

aluminum glycinate, aluminum hydroxide, cellulose gum, glycerin, methyl acrylate/2-ethylhexyl acrylate copolymer, methylparaben, nonoxynol-30, polyacrylic acid, polysorbate 80, propylene glycol, silica, sodium polyacrylate, tartaric acid, titanium dioxide, urea, water

Package/Label Principal Display Panel – Lidocaine Patch US 1ct

MAX STRENGTH

Aspercreme®with 4% LIDOCAINE
PAIN RELIEF PATCH

NUMBS AWAY PAINFAST ACTING
TARGETS NERVES
FLEXIBLE FABRIC
#1 LIDOCAINE BRAND*

PATCH

FRAGRANCE-FREE
Contains 1 Patch 3-15/16” x 5-1/2” (10 cm x 14 cm)
Pain Relieving Ointment on a Breathable Adhesive Pad

*Among OTC topical analgesics.

Dist. by Chattem, Inc., a Sanofi Company
P.O. Box 2219, Chattanooga, TN
37409-0219 USA
©2022
www.aspercreme.com Made in Japan

Label

Package/Label Principal Display Panel – Lidocaine Patch Singles US 1ct

MAX STRENGTH

Aspercreme®with 4% LIDOCAINE
PAIN RELIEF PATCH

NUMBS AWAY PAINFAST ACTING
TARGETS NERVES
FLEXIBLE FABRIC
#1 LIDOCAINE BRAND*

PATCH

FRAGRANCE-FREE
Contains 1 Patch 3-15/16” x 5-1/2” (10 cm x 14 cm)
Pain Relieving Ointment on a Breathable Adhesive Pad

*Among OTC topical analgesics

CHATTEM®
A SANOFI COMPANY
Dist. by Chattem, Inc., a Sanofi Company
P.O. Box 2219, Chattanooga, TN
37409-0219 USA ©2020
www.aspercreme.com
Made in Japan

Label